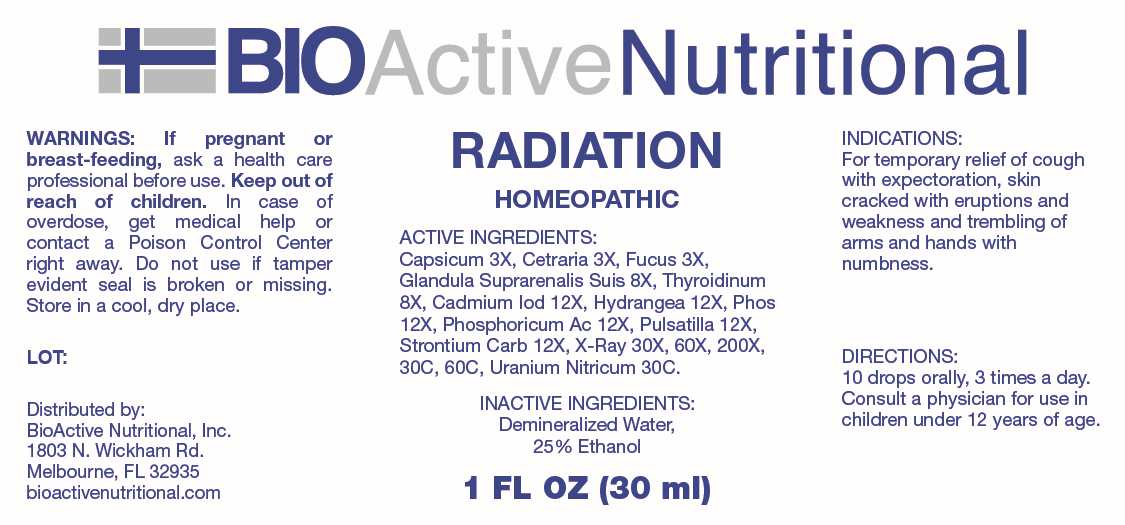 DRUG LABEL: Radiation
NDC: 43857-0646 | Form: LIQUID
Manufacturer: BioActive Nutritional
Category: homeopathic | Type: HUMAN OTC DRUG LABEL
Date: 20241114

ACTIVE INGREDIENTS: CAPSICUM 3 [hp_X]/1 mL; CETRARIA ISLANDICA WHOLE 3 [hp_X]/1 mL; FUCUS VESICULOSUS 3 [hp_X]/1 mL; SUS SCROFA ADRENAL GLAND 8 [hp_X]/1 mL; THYROID 8 [hp_X]/1 mL; CADMIUM IODIDE 12 [hp_X]/1 mL; HYDRANGEA ARBORESCENS ROOT 12 [hp_X]/1 mL; PHOSPHORIC ACID 12 [hp_X]/1 mL; PHOSPHORUS 12 [hp_X]/1 mL; PULSATILLA PRATENSIS WHOLE 12 [hp_X]/1 mL; STRONTIUM CARBONATE 12 [hp_X]/1 mL; ALCOHOL, X-RAY EXPOSED (1000 RAD) 30 [hp_X]/1 mL; URANYL NITRATE HEXAHYDRATE 30 [hp_C]/1 mL
INACTIVE INGREDIENTS: WATER; ALCOHOL

DRUG FACTS:

ACTIVE INGREDIENTS:

Capsicum Annuum 3X, Cetraria Islandica 3X, Fucus Vesiculosus 3X, Glandula Suprarenalis Suis 8X, Thyroidinum 8X, Cadmium Iodatum 12X, Hydrangea Arborescens 12X, Phosphorus 12X, Phosphoricum Acidum 12X, Pulsatilla 12X, Strontium Carbonicum 12X, X-Ray 30X, 60X, 200X, 30C, 60C, Uranium Nitricum 30C.

PURPOSE:

For temporary relief of cough with expectoration, skin cracked with eruptions and weakness and trembling of arms and hands with numbness.

WARNINGS:

If pregnant or breast-feeding, ask a health care professional before use.

Keep out of reach of children. In case of overdose, get medical help or contact a Poison Control Center right away.

Do not use if tamper evident seal is broken or missing.

Store in cool, dry place.

KEEP OUT OF REACH OF CHILDREN:

In case of overdose, get medical help or contact a Poison Control Center right away.

DIRECTIONS:

10 drops orally, 3 times a day. Consult a physician for use in children under 12 years of age.

INDICATIONS:

For temporary relief of cough with expectoration, skin cracked with eruptions and weakness and trembling of arms and hands with numbness.

INACTIVE INGREDIENTS:

Demineralized Water, 25% Ethanol

QUESTIONS:

Distributed by:

BioActive Nutritional, Inc.

1803 N. Wickham Rd.

Melbourne, FL 32935

bioactivenutritional.com

PACKAGE LABEL DISPLAY:

BIOActiveNutritional

RADIATION

HOMEOPATHIC

1 FL OZ (30 ml)